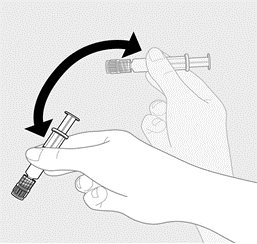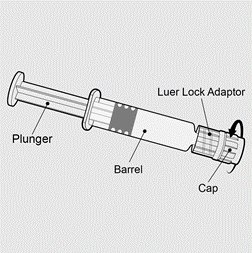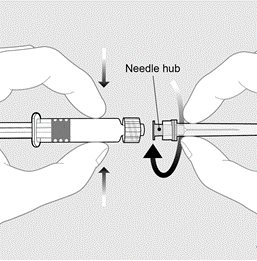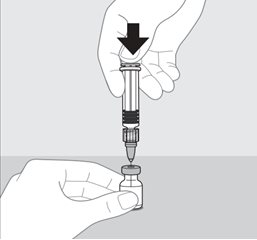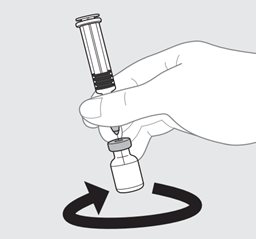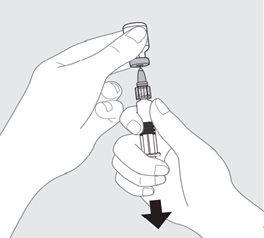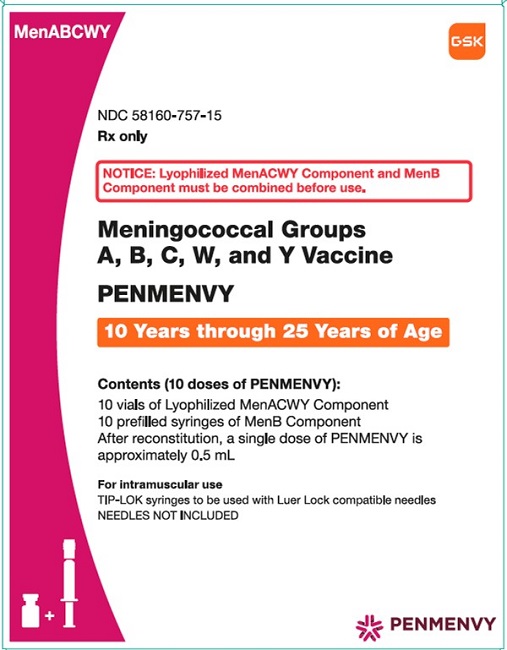 DRUG LABEL: PENMENVY
NDC: 58160-757 | Form: KIT | Route: INTRAMUSCULAR
Manufacturer: GlaxoSmithKline Biologicals SA
Category: other | Type: VACCINE LABEL
Date: 20250801

ACTIVE INGREDIENTS: NEISSERIA MENINGITIDIS GROUP A CAPSULAR OLIGOSACCHARIDE DIPHTHERIA CRM197 PROTEIN CONJUGATE ANTIGEN 10 ug/0.5 mL; NEISSERIA MENINGITIDIS GROUP C CAPSULAR OLIGOSACCHARIDE DIPHTHERIA CRM197 PROTEIN CONJUGATE ANTIGEN 5 ug/0.5 mL; NEISSERIA MENINGITIDIS GROUP W-135 CAPSULAR OLIGOSACCHARIDE DIPHTHERIA CRM197 PROTEIN CONJUGATE ANTIGEN 5 ug/0.5 mL; NEISSERIA MENINGITIDIS GROUP Y CAPSULAR OLIGOSACCHARIDE DIPHTHERIA CRM197 PROTEIN CONJUGATE ANTIGEN 5 ug/0.5 mL; NEISSERIA MENINGITIDIS GROUP B NHBA FUSION PROTEIN ANTIGEN 50 ug/0.5 mL; NEISSERIA MENINGITIDIS GROUP B FHBP FUSION PROTEIN ANTIGEN 50 ug/0.5 mL; NEISSERIA MENINGITIDIS GROUP B NADA PROTEIN ANTIGEN 50 ug/0.5 mL; NEISSERIA MENINGITIDIS GROUP B STRAIN NZ98/254 OUTER MEMBRANE VESICLE ANTIGEN 25 ug/0.5 mL
INACTIVE INGREDIENTS: ALUMINUM HYDROXIDE; SODIUM CHLORIDE; HISTIDINE; SUCROSE; WATER; DIBASIC POTASSIUM PHOSPHATE; MONOBASIC POTASSIUM PHOSPHATE

HIGHLIGHTS OF PRESCRIBING INFORMATION

These highlights do not include all the information needed to use PENMENVY safely and effectively. See full prescribing information for PENMENVY.
PENMENVY (Meningococcal Groups A, B, C, W, and Y Vaccine) for injectable suspension, for intramuscular use
Initial U.S. Approval: 2025

1 INDICATIONS AND USAGE

PENMENVY is a vaccine indicated for active immunization to prevent invasive disease caused by Neisseria meningitidis serogroups A, B, C, W, and Y in individuals 10 through 25 years of age. (1)

2 DOSAGE AND ADMINISTRATION

For intramuscular use. (2)

- Administer 2 doses (approximately 0.5 mL each) of PENMENVY 6 months apart. (2.1)
- To prepare PENMENVY, reconstitute the Lyophilized MenACWY Component with the MenB Component. (2.2)

3 DOSAGE FORMS AND STRENGTHS

For injectable suspension. A single dose after reconstitution is approximately 0.5 mL. (3)

4 CONTRAINDICATIONS

Severe allergic reaction (e.g., anaphylaxis) to a previous dose of PENMENVY, to any component of this vaccine, or to any other diphtheria toxoid-containing vaccine. (4)

5 WARNINGS AND PRECAUTIONS

Syncope (fainting) has occurred in association with administration of PENMENVY. Procedures should be in place to avoid injury from fainting. (5.2)

6 ADVERSE REACTIONS

The most commonly reported (≥10%) solicited adverse reactions after Dose 1 and Dose 2, respectively:

- in individuals aged 10 through 25 years were pain at the injection site (92% and 88%), fatigue (51% and 42%), headache (42% and 36%), myalgia (15% and 12%), nausea (15% and 10%), erythema (13% and 12%), and swelling (13% and 12%). (6.1)
- in MenACWY conjugate vaccine‑experienced individuals aged 15 through 25 years were pain at the injection site (80% and 74%), headache (41% and 33%), fatigue (40% and 33%), myalgia (15% and 13%), and nausea (15% and 12%). (6.1)

To report SUSPECTED ADVERSE REACTIONS, contact GlaxoSmithKline at 1-888-825-5249 or VAERS at 1-800-822-7967 or www.vaers.hhs.gov.

FULL PRESCRIBING INFORMATION

1 INDICATIONS AND USAGE

PENMENVY is a vaccine indicated for active immunization to prevent invasive disease caused by Neisseria meningitidis serogroups A, B, C, W, and Y in individuals 10 through 25 years of age.

2 DOSAGE AND ADMINISTRATION

For intramuscular use.

2.1 Dose and Schedule

Administer 2 doses (approximately 0.5 mL each) of PENMENVY 6 months apart.

2.2 Preparation

PENMENVY is supplied as one vial of Lyophilized MenACWY Component (powder) and one prefilled syringe of MenB Component (liquid) which must be combined before administration.

Use only the supplied MenB Component to reconstitute the Lyophilized MenACWY Component.

Figure 1. Invert the prefilled syringe of the MenB Component multiple times to form a homogeneous suspension. Do not use the prefilled syringe of the MenB Component if it cannot be resuspended.

Figure 2. Hold the syringe by the barrel. Unscrew the syringe cap by twisting it counterclockwise.

Figure 3. Connect the hub of a sterile needle to the Luer Lock Adaptor of the prefilled syringe of the MenB Component and rotate a quarter turn clockwise until it locks.

Figure 4. Cleanse the stopper of the vial containing the Lyophilized MenACWY Component. Slowly transfer the entire contents of the syringe into the vial containing the Lyophilized MenACWY Component.

Figure 5. Without removing the needle from the vial, swirl the vial gently until powder is completely dissolved. Do not invert the vial or shake vigorously.

Figure 6. After reconstitution, invert the vial and withdraw the entire contents.

PENMENVY is a white opalescent suspension. Parenteral drug products should be inspected visually for particulate matter and discoloration prior to administration, whenever solution and container permit. If either of these conditions exist, PENMENVY should not be administered.

2.3 Administration

Administer intramuscularly.

Administer PENMENVY immediately after reconstitution.

3 DOSAGE FORMS AND STRENGTHS

For injectable suspension. A single dose after reconstitution is approximately 0.5 mL.

4 CONTRAINDICATIONS

Do not administer PENMENVY to individuals with a severe allergic reaction (e.g., anaphylaxis) to a previous dose of PENMENVY, to any component of this vaccine, or to any other diphtheria toxoid-containing vaccine [see Description (11)].

5 WARNINGS AND PRECAUTIONS

5.1 Management of Allergic Reactions

Appropriate medical treatment must be immediately available to manage potential anaphylactic reactions following administration of PENMENVY.

5.2 Syncope

Syncope (fainting) has occurred in association with administration of PENMENVY. Procedures should be in place to avoid injury from fainting.

5.3 Limitation of Vaccine Effectiveness

Vaccination with PENMENVY may not protect all vaccine recipients. PENMENVY may not provide protection against all meningococcal serogroup B strains [see Clinical Pharmacology (12.1)].

5.4 Altered Immunocompetence

Reduced Immune Response

Immunocompromised persons, including those receiving immunosuppressive therapy, may have reduced immune responses to PENMENVY.

Complement Deficiency

Persons with certain complement deficiencies and persons receiving treatment that inhibits terminal complement activation are at increased risk for invasive disease caused by N. meningitidis, including disease caused by serogroups A, B, C, W, and Y, even if they develop antibodies following vaccination with PENMENVY [see Clinical Pharmacology (12.1)].

5.5 Guillain-Barré Syndrome

Guillain‑Barré syndrome (GBS) has been reported in temporal relationship following administration of a U.S.‑licensed meningococcal quadrivalent polysaccharide conjugate vaccine. The decision by the healthcare professional to administer PENMENVY to persons with a history of GBS should take into account the expected benefits and potential risks.

6 ADVERSE REACTIONS

The most commonly reported (≥10%) solicited adverse reactions after Dose 1 and Dose 2, respectively, in Study 1 in participants aged 10 through 25 years (87% of whom were MenACWY conjugate vaccine‑naïve) were pain at the injection site (92% and 88%), fatigue (51% and 42%), headache (42% and 36%), myalgia (15% and 12%), nausea (15% and 10%), erythema (13% and 12%), and swelling (13% and 12%).

The most commonly reported (≥10%) solicited adverse reactions after Dose 1 and Dose 2, respectively, in Study 2 in MenACWY conjugate vaccine‑experienced participants aged 15 through 25 years were pain at the injection site (80% and 74%), headache (41% and 33%), fatigue (40% and 33%), myalgia (15% and 13%), and nausea (15% and 12%).

6.1 Clinical Trials Experience

Because clinical trials are conducted under widely varying conditions, adverse reaction rates observed in the clinical trials of a vaccine cannot be directly compared with rates in the clinical trials of another vaccine and may not reflect the rates observed in practice.

The safety of PENMENVY was evaluated in 12 clinical studies^1 in which a total of 3,718 participants received at least one dose of PENMENVY. Participants in Study 1 (aged 10 through 25 years) and Study 2 (aged 15 through 25 years) were scheduled to receive PENMENVY according to the approved dosing schedule (2 doses administered 6 months apart). Participants in the other studies may have received PENMENVY according to unapproved dosing schedules. Across the 12 studies, 2,969 participants received at least 1 dose of BEXSERO (Meningococcal Group B Vaccine) and 361 participants received a single dose of MENVEO [Meningococcal (Groups A, C, Y, and W‑135) Oligosaccharide Diphtheria CRM197 Conjugate Vaccine]. Across the studies, the median age was 16 years, males comprised 46%, and 86% of participants were White, 6% were Black, 4% were Asian, and 4% were of other racial groups. In these studies, 13% of participants were Hispanic. Approximately 35% of participants were from the U.S.

Nine of the 12 studies (including Study 1 and Study 2) collected non‑serious unsolicited adverse events through 30 days after each vaccination, and the other 3 studies collected these events through 7 days after each vaccination. All studies collected serious adverse events through at least 1 month following the last vaccination. Study 1 and Study 2 collected serious adverse events through 12 months following the first vaccination and at least 5 months following the last vaccination.

Study 1 (NCT04502693) was a randomized, controlled, observer‑blind study conducted in 7 countries (U.S., Australia, Canada, Czech Republic, Estonia, Finland, and Turkey). In this study, 1,657 participants aged 10 through 25 years received at least 1 dose of PENMENVY. Participants were scheduled to receive 2 doses of PENMENVY 6 months apart. Separate groups received BEXSERO either as a 0‑, 2‑, 6‑month schedule or 0‑, 6‑month schedule. A single dose of MENVEO was administered 1 month after the third dose in the 0‑, 2‑, 6‑month group and 2 months after the first dose of BEXSERO in the 0‑, 6‑month group (these participants received saline placebo at month 7). A separate group received a single dose of MENVEO at month 0, a saline placebo dose at month 2, and doses of BEXSERO at months 6 and 7 (an unapproved BEXSERO dosing regimen). All participants were MenB vaccine‑naïve. Both MenACWY conjugate vaccine‑naïve (87%) and MenACWY conjugate vaccine‑experienced (13%, vaccinated at least 4 years prior to study enrollment) participants were part of the study. The median age was 16 years, males comprised 47%, and 89% of participants were White, 5% were Asian, 4% were Black, and 2% were of other racial groups. Among study participants, 5% were Hispanic. Approximately 30% of participants were from the U.S.

Study 2 (NCT04707391) was a randomized, controlled, observer‑blind study conducted in 4 countries (U.S., Australia, Canada, and Argentina). In this study, 626 participants aged 15 through 25 years received at least 1 dose of PENMENVY. All participants were MenACWY conjugate vaccine‑experienced (vaccinated at least 4 years prior to study enrollment). A separate group received a single dose of MENVEO followed 6 months later by 2 doses of BEXSERO administered 1 month apart (an unapproved BEXSERO dosing regimen). In this study, the median age was 16 years, males comprised 47%, and 75% of participants were White, 14% were Black, 6% were of other racial groups, and 4% were Asian. Among study participants, 30% were Hispanic. Approximately 59% of participants were from the U.S.

Solicited Adverse Reactions

In Study 1, solicited local and systemic adverse reactions were collected for 7 days after study vaccination using electronic diaries. The rates of local and systemic adverse reactions reported in Study 1 among participants aged 10 through 25 years following each dose of PENMENVY administered 6 months apart, each dose of BEXSERO administered 6 months apart, or a single dose of MENVEO are presented in Table 1.

Table 1. Percentage of Participants Aged 10 Through 25 Years Reporting Solicited Local and Systemic Adverse Reactions Within 7 Days of PENMENVY, BEXSERO, or MENVEO, by Dose in Study 1
 |  | PENMENVY; % |  | BEXSERO; % |  | MENVEO; %
Solicited Reactiona |  | Dose 1 | Dose 2 | Dose 1 | Dose 2 | Dose 1
Solicited Reactiona |  | N = 1,638 | N = 1,428 | N = 894 | N = 759 | N = 178
Local Adverse Reactions
Pain | Any | 92 | 88 | 92 | 89 | 38
Pain | Severe | 6 | 7 | 6 | 8 | 0
Erythema | Any | 13 | 12 | 10 | 12 | 6
Erythema | Severe | 1 | 2 | 1 | 1 | 1
Swelling | Any | 13 | 12 | 10 | 11 | 6
Swelling | Severe | 2 | 2 | 1 | 2 | 1
Induration | Any | 9 | 8 | 7 | 8 | 4
Induration | Severe | 1 | 1 | 2 | 1 | 0
Systemic Adverse Reactions
Fatigue | Any | 51 | 42 | 46 | 45 | 44
Fatigue | Severe | 3 | 3 | 1 | 3 | 2
Nausea | Any | 15 | 10 | 12 | 11 | 15
Nausea | Severe | 0.3 | 0.3 | 1 | 0.4 | 1
Myalgia | Any | 15 | 12 | 12 | 14 | 7
Myalgia | Severe | 1 | 1 | 1 | 0.4 | 0
Arthralgia | Any | 8 | 7 | 8 | 7 | 10
Arthralgia | Severe | 1 | 0.4 | 0.3 | 0 | 0
Headache | Any | 42 | 36 | 37 | 37 | 39
Headache | Severe | 2 | 1 | 1 | 1 | 2
Fever | Any | 3 | 2 | 2 | 3 | 2
Fever | Severe | 0.1 | 0.1 | 0.1 | 0 | 1
Study 1: NCT04502693.
N = Number of participants in Solicited Safety Set (participants who received at least 1 dose of study vaccine who reported solicited safety data).
a Erythema, swelling, and induration: Any (≥25 mm); Severe (>100 mm). Pain, fatigue, nausea, myalgia, arthralgia, headache: Any includes Mild (transient with no limitation in normal daily activity), Moderate (some limitation in normal daily activity), and Severe (unable to perform normal daily activity). Fever: Any (≥38.0°C/100.4°F); Severe (≥40.0°C/104.0°F).

In Study 2, solicited local and systemic adverse reactions were collected for 7 days after study vaccination using electronic diaries. The rates of local and systemic adverse reactions reported in Study 2 among participants aged 15 through 25 years following each dose of PENMENVY administered 6 months apart or a single dose of MENVEO are presented in Table 2.

Table 2. Percentage of Participants Aged 15 Through 25 Years Reporting Solicited Local and Systemic Adverse Reactions Within 7 Days of PENMENVY or MENVEO, by Dose in Study 2
 |  | PENMENVY; % |  | MENVEO; %
Solicited Reactiona |  | Dose 1 | Dose 2 | Dose 1
Solicited Reactiona |  | N = 608 | N = 505-507 | N = 600-601
Local Adverse Reactions
Pain | Any | 80 | 74 | 32
Pain | Severe | 3 | 3 | 0.3
Erythema | Any | 5 | 6 | 2
Erythema | Severe | 0.5 | 0.6 | 0
Swelling | Any | 4 | 6 | 2
Swelling | Severe | 0.3 | 0.6 | 0.3
Induration | Any | 4 | 5 | 2
Induration | Severe | 2 | 0.6 | 0.2
Systemic Adverse Reactions
Fatigue | Any | 40 | 33 | 37
Fatigue | Severe | 1 | 2 | 0.5
Nausea | Any | 15 | 12 | 13
Nausea | Severe | 0.5 | 1 | 0.7
Myalgia | Any | 15 | 13 | 11
Myalgia | Severe | 0.2 | 0.4 | 0.3
Arthralgia | Any | 7 | 6 | 8
Arthralgia | Severe | 0 | 0.2 | 0
Headache | Any | 41 | 33 | 35
Headache | Severe | 1 | 1 | 0.7
Fever | Any | 2 | 2 | 1
Fever | Severe | 0.2 | 0.4 | 0.2
Study 2: NCT04707391.
N = Number of participants in Solicited Safety Set (participants who received at least 1 dose of study vaccine who reported solicited safety data).
a Erythema, swelling, and induration: Any (≥25 mm); Severe (>100 mm). Pain, fatigue, nausea, myalgia, arthralgia, headache: Any includes Mild (transient with no limitation in normal daily activity), Moderate (some limitation in normal daily activity), and Severe (unable to perform normal daily activity). Fever: Any (≥38.0°C/100.4°F); Severe (≥40.0°C/104.0°F).

Unsolicited Adverse Events

In an analysis across the 12 studies, unsolicited adverse events that were reported in participants who received PENMENVY (N = 3,718) and were determined to be causally related included syncope, dizziness, and pre‑syncope (0.9%); lymphadenopathy (0.2%); and hypersensitivity (0.1%). The onset of syncope, dizziness, pre‑syncope, and lymphadenopathy ranged from 1 to 30 days and the onset of hypersensitivity ranged from 9 to 27 days.

Serious Adverse Events

In Study 1, serious adverse events that occurred through 12 months following the first vaccination and at least 5 months following the last vaccination were reported by 1.5% of participants in the PENMENVY group (N = 1,648), 2.4% of participants in the group who received BEXSERO as a 0‑, 6‑month schedule with a dose of MENVEO at month 2 (N = 900), and 2.8% of participants in the group who received MENVEO at month 0 and BEXSERO at months 6 and 7 (N = 178).

In Study 2, serious adverse events that occurred through 12 months following the first vaccination and at least 5 months following the last vaccination were reported by 2.9% of participants in the PENMENVY group (N = 626) and 1.1% of participants in the group who received MENVEO at month 0 and BEXSERO at months 6 and 7 (N = 621).

Across the 12 clinical studies, serious adverse events were reported within 30 days after any dose by 0.6% of participants who received PENMENVY (N = 3,718), 0.4% of participants who received BEXSERO (N = 2,969), and 0.3% of participants who received MENVEO (N = 361). Two serious adverse events reported following administration of PENMENVY were assessed as vaccine‑related and are described below.

In Study 3,^1 connective tissue disorder was reported in an adolescent participant who developed 3 episodes of petechiae (7 days after PENMENVY Dose 1, 18 days after PENMENVY Dose 2 [given 1 month after Dose 1], and 17 days after HAVRIX [Hepatitis A Vaccine]) and was diagnosed with a connective tissue disorder 44 days after PENMENVY Dose 2.

In Study 3,^1 seizures were reported in an adult participant with onset 9 hours after PENMENVY Dose 1.

6.2 Postmarketing Experience

The following adverse reactions have been reported during postapproval use of BEXSERO or MENVEO. The postmarketing safety experience with BEXSERO and MENVEO is relevant because PENMENVY contains the same group A, C, W, and Y CRM197‑conjugated oligosaccharide components and MenB recombinant protein components. Because these reactions were reported voluntarily from a population of uncertain size, it is not always possible to reliably estimate their frequency or establish a causal relationship to the vaccine exposure.

Blood and Lymphatic System Disorders

Lymphadenopathy.a,b

Ear and Labyrinth Disorders

Hearing impaired,b ear pain,b vertigo,b vestibular disorder.b

Eye Disorders

Eyelid ptosis.b

General Disorders and Administration Site Conditions

Injection site reactions (including injection site pruritus,b pain,b erythema,b inflammation,b swelling,b extensive swelling of the vaccinated limb,a,b blisters at or around the injection site,a and injection site nodule which may persist for more than 1 montha), fatigue,b malaise,b pyrexia.b

Immune System Disorders

Allergic reactions,a anaphylactic reactions,a eye swelling,a rash,a hypersensitivity reactions,b anaphylaxis.b

Infections and Infestations

Vaccination site cellulitis.b

Injury, Poisoning, and Procedural Complications

Fall,b head injury.b

Investigation

Alanine aminotransferase increased,b body temperature increased.b

Musculoskeletal and Connective Tissue Disorders

Arthralgia,b bone pain.b

Nervous System Disorders

Dizziness,b syncope,a,b tonic convulsion,b headache,b facial paresis,b balance disorder,b vasovagal responses to injection.a

Respiratory, Thoracic, and Mediastinal Disorders

Oropharyngeal pain.b

Skin and Subcutaneous Tissue Disorders

Skin exfoliation.b

a Observed with BEXSERO.

b Observed with MENVEO.

Postmarketing Observational Safety Study

In a postmarketing observational safety study conducted in a U.S. health maintenance organization, data from electronic health records of 48,899 persons aged 11 through 21 years were used to evaluate pre‑specified events of interest following vaccination with MENVEO. Using a self‑controlled case series method, Bell’s palsy showed a statistically significant increased risk in the period 1 to 84 days post vaccination compared with the control period, with an overall adjusted relative incidence of 2.9 (95% CI: 1.1‑7.5). Among the 8 reported cases of Bell’s palsy, 6 cases occurred in persons who received MENVEO concomitantly with one or more of the following vaccines: Tetanus Toxoid, Reduced Diphtheria Toxoid and Acellular Pertussis Vaccine Adsorbed (Tdap), a human papillomavirus vaccine, and Influenza Vaccine. All reported Bell’s palsy cases resolved.

8 USE IN SPECIFIC POPULATIONS

8.1 Pregnancy

Risk Summary

All pregnancies have a risk of birth defect, loss, or other adverse outcomes. In the U.S. general population, the estimated background risk of major birth defects and miscarriage in clinically recognized pregnancies is 2% to 4% and 15% to 20%, respectively.

There are no adequate and well-controlled studies of PENMENVY in pregnant women. Available human data on PENMENVY administered to pregnant women are insufficient to inform vaccine-associated risks in pregnancy.

A developmental toxicity study was performed in female rabbits administered a dose of PENMENVY (0.5 mL) on 5 occasions, three times prior to mating and twice during gestation. This study revealed no vaccine‑related effects on female fertility, fetal development or postnatal development (see Data).

Data

Animal Data: In a developmental toxicity study, female rabbits were administered a dose of PENMENVY (0.5 mL) by intramuscular injection on 5 occasions: 35, 21 and 7 days prior to mating, and on gestation days 7 and 20. No vaccine‑related adverse effects on female fertility, fetal development, or postnatal development were reported in the study.

8.2 Lactation

Risk Summary

It is not known whether the vaccine components of PENMENVY are excreted in human milk. Available data are not sufficient to assess the effects of PENMENVY on the breastfed infant or on milk production/excretion. The developmental and health benefits of breastfeeding should be considered along with the mother’s clinical need for PENMENVY and any potential adverse effects on the breastfed child from PENMENVY or from the underlying maternal condition. For preventive vaccines, the underlying maternal condition is susceptibility to disease prevented by the vaccine.

8.4 Pediatric Use

Safety and effectiveness of PENMENVY have not been established in children younger than 10 years of age.

8.5 Geriatric Use

Safety and effectiveness of PENMENVY in adults aged 65 years and older have not been established.

11 DESCRIPTION

PENMENVY (Meningococcal Groups A, B, C, W, and Y Vaccine) is a sterile injectable suspension for intramuscular use. The vaccine is supplied as one vial of Lyophilized MenACWY Component which is reconstituted at the time of use with the accompanying prefilled syringe of MenB Component.

The Lyophilized MenACWY Component contains N. meningitidis serogroups A, C, W, and Y oligosaccharides conjugated individually to Corynebacterium diphtheriae CRM197 protein. The polysaccharides are produced by bacterial fermentation of N. meningitidis serogroups A, C, W, or Y. N. meningitidis serogroup A, C, W, and Y strains are each cultured and grown on Franz Complete medium and treated with formaldehyde. MenA, MenW, and MenY polysaccharides are purified by several steps, including extraction, filtration, and precipitation. MenC polysaccharide is purified by a combination of extraction, chromatography, and precipitation steps.

The protein carrier (CRM197) is produced by bacterial fermentation and is purified by a series of chromatography and ultrafiltration steps. The C. diphtheriae is cultured and grown on CY medium containing yeast extracts and amino acids.

The oligosaccharides are prepared for conjugation from the purified polysaccharides which are processed by hydrolysis, sizing, and reductive amination. After activation, each oligosaccharide is covalently linked to the CRM197 protein. The resulting glycoconjugates are purified to yield the four drug substances, which are formulated with sucrose and phosphate and lyophilized to form the Lyophilized MenACWY Component. The Lyophilized MenACWY Component is a white to off‑white lyophilized cake.

The MenB Component contains recombinant N. meningitidis proteins Neisseria adhesin A (NadA), Neisserial Heparin Binding Antigen (NHBA), and factor H binding protein (fHbp), and Outer Membrane Vesicles (OMV). The NadA component is a fragment of the full‑length protein derived from N. meningitidis strain 2996 (peptide 8 variant 2/3).^2 The NHBA component is a recombinant fusion protein comprised of NHBA (peptide 2)^2 and accessory protein 953 derived from N. meningitidis strains NZ98/254 and 2996, respectively. The fHbp component is a recombinant fusion protein comprised of fHbp (variant 1.1)^2 and the accessory protein 936 derived from N. meningitidis strains MC58 and 2996, respectively. These 3 recombinant proteins are individually produced in Escherichia coli and purified through a series of column chromatography steps. The OMV antigenic component is produced by fermentation of N. meningitidis strain NZ98/254 (expressing outer membrane protein Porin A [PorA] serosubtype P1.4),^3 followed by inactivation of the bacteria by deoxycholate, which also mediates vesicle formation. The antigens are adsorbed onto aluminum hydroxide. The MenB Component is a white opalescent suspension.

After reconstitution, each approximately 0.5‑mL dose contains 10 mcg MenA oligosaccharide; 5 mcg of each of MenC, MenW, and MenY oligosaccharides; 25.9 to 64.1 mcg CRM197 protein; 50 mcg each of recombinant proteins NadA, NHBA, and fHbp; and 25 mcg of OMV. Each dose also contains 1.5 mg aluminum hydroxide (0.5 mg of Al^3+), 3.125 mg sodium chloride, 0.776 mg histidine, 22.5 mg sucrose, and ≤0.7 mg potassium phosphate salts. Each dose contains less than 0.01 mcg kanamycin (by calculation). Residual formaldehyde per dose is estimated to be not more than 0.30 mcg. After reconstitution, PENMENVY is a white opalescent suspension.

The tip cap and rubber plunger of the prefilled syringe and the stopper of the vial are not made with natural rubber latex.

PENMENVY does not contain preservatives.

12 CLINICAL PHARMACOLOGY

12.1 Mechanism of Action

Protection against invasive meningococcal disease is conferred mainly by complement‑mediated antibody‑dependent killing of N. meningitidis strains.^4 Immunization with PENMENVY is intended to stimulate the production of antibodies with bactericidal activity specific to the capsular polysaccharides of N. meningitidis serogroups A, C, W, and Y and to the protein antigens NHBA, NadA, fHbp and OMV expressed by serogroup B meningococcal strains.

NHBA, NadA, and fHbp are proteins found on the surface of meningococci and contribute to the ability of the bacterium to cause disease. OMV derived from the bacterial outer membrane contains PorA and other surface proteins. The susceptibility of serogroup B meningococci to complement‑mediated antibody‑dependent killing following vaccination with PENMENVY is dependent on both the antigenic similarity of the bacterial and vaccine antigens, as well as the amount of antigen expressed on the surface of the invading meningococci.

13 NONCLINICAL TOXICOLOGY

13.1 Carcinogenesis, Mutagenesis, Impairment of Fertility

PENMENVY has not been evaluated for carcinogenic or mutagenic potential or impairment of male fertility in animals.

14 CLINICAL STUDIES

The effectiveness of PENMENVY was assessed by measuring serum bactericidal activity (SBA) in an assay that used endogenous complement preserved in the serum samples collected from study participants (enc-hSBA) and an assay that used an exogenous source of human complement (hSBA).

The enc-hSBA assay was used to assess effectiveness against diverse N. meningitidis serogroup B strains. Participants’ sera were tested for the presence or absence of bactericidal activity to measure breadth of immune response against a panel of 110 diverse U.S. disease-causing N. meningitidis serogroup B strains that were collected between 2000 and 2008. The panel includes most antigen types found among serogroup B isolates circulating in the U.S. between 2000 and 2017, and includes some strains with genetic profiles characterized as hypervirulent. Each participant’s serum was tested at a four-fold dilution against a maximum of 35 strains randomly selected from the panel.

The hSBA assay measured bactericidal activity in participants’ sera against the 5 N. meningitidis serogroups. For serogroup B, four meningococcal serogroup B indicator strains expressing different antigens (fHbp, NadA, NHBA and OMV) were utilized. For serogroups A, C, W, and Y, one strain was utilized per serogroup.

Breadth of Immune Response Elicited by PENMENVY Against Serogroup B (enc-hSBA Assay)

Study 1 evaluated enc-hSBA responses in participants aged 10 through 25 years at one month after Dose 2 of PENMENVY, after Dose 2 of the BEXSERO 0-, 6-month schedule, after Dose 3 of the BEXSERO 0-, 2-, 6-month schedule, and after a single dose of MENVEO, using responder-based and test-based analyses.

Responder-based analyses (Table 3) evaluated the percentages of participants whose sera killed ≥70% of the tested strains.

Table 3. Percentage of Participants Whose Sera Killed ≥70% of Meningococcal Serogroup B Strains Testeda (Responder-Based) Following PENMENVY and BEXSERO, Study 1b
Groupc | N | % Respondersd; (95% CI)
PENMENVY | 817 | 84.1; (81.4e, 86.5)
BEXSERO (0, 6 Months) | 813 | 89.8; (87.5, 91.8)
BEXSERO (0, 2, 6 Months) | 790 | 93.4; (91.5, 95.0)
Study 1: NCT04502693.
N = Number of participants, CI = Confidence interval.
a Each participant’s serum was tested using the enc‑hSBA assay for bactericidal activity (yes/no) against a maximum of 35 strains randomly selected from the 110‑strain panel.
b Full Analysis Set includes all participants who received at least 1 dose of the study treatment and have post‑vaccination immunogenicity data.
c enc‑hSBA response was measured one month after Dose 2 of PENMENVY, one month after Dose 2 of BEXSERO (0‑, 6‑month schedule), or one month after Dose 3 of BEXSERO (0‑, 2‑, 6‑month schedule).
d % Responders is defined as percentages of participants whose serum kills ≥70% of strains tested using the enc‑hSBA assay.
e Predefined criterion (lower limit of the 2‑sided 95% CI >65%) met. CI calculated using Clopper‑Pearson method.

Of the approximately 35 serogroup B strains tested per participant in the enc‑hSBA assay at 1 month following vaccination, the median percentage killed by each participant’s serum was 85.3% (25th percentile, 74.3%; 75th percentile, 91.4%) after Dose 2 of PENMENVY; 88.2% (25th percentile, 80.0%; 75th percentile, 94.3%) after Dose 2 of the 0‑, 6‑month BEXSERO schedule; 88.6% (25th percentile, 80.0%; 75th percentile, 94.3%) after Dose 3 of the 0‑, 2‑, 6‑month BEXSERO schedule; and 17.1% (25th percentile, 11.1%; 75th percentile, 26.7%) after MENVEO.

Test‑based analyses evaluated the percentage of tests with bactericidal activity. The non‑inferiority criterion was met for the percentage of tests with bactericidal activity following PENMENVY compared with BEXSERO (0‑, 6‑month schedule) (Table 4).

Table 4. Percentages of Testsa With Bactericidal Activity Against Meningococcal Serogroup B Strains Following PENMENVY, BEXSERO, and MENVEO, Study 1b
Groupc | Number of Participants | % of Tests with Bactericidal Activity; (n/N) | Percent Difference PENMENVY –; BEXSERO (0, 6 Months); (95% CI)d
PENMENVY | 754 | 82.5; (21,222 / 25,715) | -3.0; (-3.7e, -2.4)
BEXSERO; (0, 6 Months) | 764 | 85.6; (22,365 / 26,142) | -3.0; (-3.7e, -2.4)
BEXSERO; (0, 2, 6 Months) | 747 | 86.7; (22,184 / 25,596) | -
MENVEO | 133 | 21.0; (918 / 4,374) | -
Study 1: NCT04502693.
n = Number of tests with bactericidal activity, N = Total number of tests, CI = Confidence interval.
a Each test qualitatively assessed (yes/no) the bactericidal activity of one participant’s serum using the enc‑hSBA assay against one of the 110 U.S. meningococcal serogroup B strains. Each participant’s serum was tested against a maximum of 35 strains randomly selected from the 110‑strain panel.
b Per Protocol Set includes all participants in the Full Analysis Set minus participants with protocol deviations that lead to exclusion from the Per Protocol Set.
c enc‑hSBA responses were measured one month after Dose 2 of PENMENVY, one month after Dose 2 of BEXSERO (0‑, 6‑month schedule), one month after Dose 3 of BEXSERO (0‑, 2‑, 6‑month schedule), or one month after a single dose of MENVEO.
d Predefined non‑inferiority criterion was defined as lower limit of the 2‑sided 95% CI for vaccine group differences [PENMENVY minus BEXSERO (0‑, 6‑month schedule)] above -5%. Criterion for non‑inferiority of PENMENVY to more than one comparator with respect to percent of tests with bactericidal activity was not pre‑specified.
e Met predefined non‑inferiority criterion. CI calculated using Miettinen and Nurminen method.

For each individual strain in the 110‑strain panel, the percentage of tests with bactericidal activity following PENMENVY ranged from 2% to 100%; the median was 97% (25th percentile, 70%; 75th percentile, 99%). For each individual strain, the percentage of tests with bactericidal activity following BEXSERO ranged from 4% to 100%; the median was 97% (25th percentile, 80%; 75th percentile, 99%) for the 0‑, 6‑month schedule and 98% (25th percentile, 85%; 75th percentile, 99%) for the 0‑, 2‑, 6‑month schedule. For each individual strain, the percentage of tests with bactericidal activity following MENVEO ranged from 0% to 100%; the median was 12% (25th percentile, 3%; 75th percentile, 28%).

Immune Response to PENMENVY Against Serogroup B (hSBA Assay)

In Study 1, immune responses in participants aged 10 through 25 years were measured at one month after Dose 2 of PENMENVY, after Dose 2 of the BEXSERO 0‑, 6‑month schedule, and after Dose 3 of the BEXSERO 0‑, 2‑, 6‑month schedule with hSBA assays using indicator strains representative of each of the 4 antigenic components of PENMENVY (fHbp, NadA, NHBA, and OMV). The percentages of participants who achieved a 4‑fold or greater increase in hSBA titer for each of the 4 strains (seroresponse) and the percentages of participants with a titer greater than or equal to the lower limit of quantitation (LLOQ) of the assay for all 4 strains (composite response) are shown in Table 5.

Non‑inferiority of PENMENVY compared with BEXSERO (0‑, 6‑month schedule) for the proportion of participants with a seroresponse was demonstrated for meningococcal serogroup B indicator strains for fHbp and NadA, but not for indicator strains for NHBA or OMV (Table 5).

Table 5. Percentages of Participants With hSBA Seroresponse and Composite Response Against Meningococcal Serogroup B Indicator Strains Following PENMENVY and BEXSERO, Study 1a
% Seroresponse
(95% CI)b,c,d,e
Antigen; (Indicator Strain) | PENMENVY | BEXSERO; (0, 6 Months) | Percent Difference; PENMENVY –; BEXSERO
fHbp; (M14459) | N = 675; 73.2; (69.7, 76.5) | N = 654; 78.1; (74.8, 81.2) | -5.0; (-9.6f, -0.3)
NadA; (96217) | N = 671; 92.7; (90.5, 94.5) | N = 655; 95.9; (94.1, 97.3) | -3.2; (-5.8f, -0.7)
NHBA; (M13520) | N = 678; 61.8; (58.0, 65.5) | N = 659; 69.7; (66.0, 73.1) | -7.9; (-12.9g, -2.8)
OMV; (NZ98/254) | N = 642; 42.2; (38.4, 46.1) | N = 624; 58.3; (54.4, 62.2) | -16.1; (-21.5g, -10.6)
% Composite Response
(95% CI)d,e,h,i,j
Timepoint | PENMENVY | BEXSERO; (0, 6 Months) | -
Baseline; (pre‑vaccination) | N = 747; 1.1; (0.5, 2.1) | N = 708; 0.6; (0.2, 1.4) | -
1 Month; post‑dose 2 | N = 707; 70.0; (66.5, 73.4) | N = 683; 80.1; (76.9, 83.0) | -
Study 1: NCT04502693.
hSBA = Serum bactericidal activity measured using an exogenous source of human complement, CI = Confidence interval, fHbp = Factor H binding protein, N = Number of participants, NadA = Neisseria adhesin A, NHBA = Neisserial Heparin Binding Antigen, OMV = Outer Membrane Vesicles, LOD = Limit of detection, LLOQ = Lower limit of quantitation.
a hSBA responses were measured one month after Dose 2 of PENMENVY or one month after Dose 2 of BEXSERO (0‑, 6‑month schedule).
b Per Protocol Set includes all participants in the Full Analysis Set minus participants with protocol deviations that lead to exclusion from the Per Protocol Set.
c Seroresponse is defined as: a post‑vaccination hSBA titer at least 4‑fold the LOD or ≥LLOQ, whichever is greater, for participants with pre‑vaccination hSBA titer <LOD, a post‑vaccination hSBA titer at least 4‑fold the LLOQ for participants with pre‑vaccination hSBA titer ≥LOD and <LLOQ, and a post‑vaccination hSBA titer at least 4‑fold the pre‑vaccination hSBA titer for participants with pre‑vaccination hSBA titer ≥LLOQ.
d LOD = 4 for fHbp; 6 for NadA; 4 for NHBA; 4 for OMV. LLOQ = 5 for fHbp; 14 for NadA; 6 for NHBA; 6 for OMV.
e CI calculated using Clopper‑Pearson method.
f Met predefined non‑inferiority criterion (lower limit of the 2‑sided 95% CI above -10% for vaccine group differences [PENMENVY minus BEXSERO (0‑, 6‑month schedule)]). CI calculated using Miettinen and Nurminen method.
g Did not meet predefined non‑inferiority criterion (lower limit of the 2‑sided 95% CI below -10% for vaccine group differences [PENMENVY minus BEXSERO (0‑, 6‑month schedule)]). CI calculated using Miettinen and Nurminen method.
h Full Analysis Set includes all participants who received at least 1 dose of the study treatment and have post‑vaccination immunogenicity data.
i Composite Response is defined as hSBA ≥LLOQ for all 4 meningococcal B indicator strains.
j Criterion for non‑inferiority of PENMENVY to BEXSERO (0‑, 6‑month schedule) with respect to the composite response was not pre‑specified.

The percentages of participants with seroresponses after Dose 3 of BEXSERO (0‑, 2‑, 6‑month schedule) were 81.1% (95% CI: 77.8, 84.1) for fHbp; 98.8% (95% CI: 97.6, 99.5) for NadA; 66.4% (95% CI: 62.6, 70.0) for NHBA; 56.4% (95% CI: 52.3, 60.4) for OMV (Per Protocol Set). The composite response at baseline and 1 month after dose 3 was 1.1% (95% CI: 0.5, 2.2.) and 81.5% (95% CI: 78.3, 84.4), respectively (Full Analysis Set).

Immune Response to PENMENVY Against Serogroups A, C, W, and Y (hSBA Assay)

The serum bactericidal antibody responses were measured using hSBA assay against serogroups A, C, W, and Y in MenACWY vaccine‑naïve participants in Study 1 and in MenACWY vaccine‑experienced participants in Study 2.

The non‑inferiority criteria for the percentages of participants achieving a seroresponse against each of the four serogroups A, C, W, and Y were met at one month after Dose 2 of PENMENVY compared to a single dose of MENVEO in MenACWY vaccine‑naïve participants (Table 6) and in MenACWY vaccine‑experienced participants (Table 7).

Table 6. Percentages of Participants With hSBA Seroresponses Against Meningococcal Serogroups A, C, W, and Y Strains Following PENMENVY and MENVEO, MenACWY-Naïve, Study 1a,b
Serogroup | % Seroresponsec,d; (95% CI)e |  | Percent Difference PENMENVY –; MENVEO; (95% CI)
Serogroup | PENMENVY | MENVEO | Percent Difference PENMENVY –; MENVEO; (95% CI)
A | N = 1,170; 96.8; (95.7, 97.8) | N = 111; 85.6; (77.6, 91.5) | 11.3; (5.8f, 19.0)
C | N = 1,189; 97.2; (96.1, 98.1) | N = 114; 50.0; (40.5, 59.5) | 47.2; (38.1f, 56.3)
W | N = 1,185; 97.0; (95.9, 97.9) | N = 115; 61.7; (52.2, 70.6) | 35.3; (26.9f, 44.5)
Y | N = 1,196; 96.7; (95.6, 97.7) | N = 119; 69.7; (60.7, 77.8) | 27.0; (19.4f, 35.8)
Study 1: NCT04502693.
hSBA = Serum bactericidal activity measured using an exogenous source of human complement, CI = Confidence interval, N = Number of participants, LOD = Limit of detection, LLOQ = Lower limit of quantitation.
a Per Protocol Set includes all participants in the Full Analysis Set minus participants with protocol deviations that lead to exclusion from the Per Protocol Set.
b Immune responses were measured one month after Dose 2 of PENMENVY or a single dose of MENVEO relative to baseline.
c Seroresponse is defined as: a post‑vaccination hSBA titer at least 4‑fold the LOD for participants with pre‑vaccination hSBA titer <LOD, a post‑vaccination hSBA titer at least 4‑fold the LLOQ for participants with pre‑vaccination hSBA titer ≥LOD and <LLOQ, and a post‑vaccination hSBA titer at least 4‑fold the pre‑vaccination hSBA titer for participants with pre‑vaccination hSBA titer ≥LLOQ.
d LOD = 5 for MenA; 4 for MenC, MenW, and MenY. LLOQ = 12 for MenA; 8 for MenC; 8 for MenW; 10 for MenY.
e CI calculated using Clopper‑Pearson method.
f Met predefined non‑inferiority criterion (lower limit of the 2‑sided 95% CI above -10% for vaccine group differences [PENMENVY minus MENVEO]). CI calculated using Miettinen and Nurminen method.

Table 7. Percentages of Participants With hSBA Seroresponses Against Meningococcal Serogroups A, C, W, and Y Strains Following PENMENVY and MENVEO, MenACWY-Experienced, Study 2a,b
Serogroup | % Seroresponsec,d; (95% CI)e |  | Percent Difference; PENMENVY –; MENVEO; (95% CI)
Serogroup | PENMENVY | MENVEO | Percent Difference; PENMENVY –; MENVEO; (95% CI)
A | N = 168; 95.8; (91.6, 98.3) | N = 501; 95.2; (93.0, 96.9) | 0.6; (-3.8f, 3.8)
C | N = 181; 94.5; (90.1, 97.3) | N = 546; 94.0; (91.6, 95.8) | 0.5; (-4.1f, 4.0)
W | N = 181; 95.6; (91.5, 98.1) | N = 544; 93.9; (91.6, 95.8) | 1.6; (-2.7f, 4.9)
Y | N = 180; 95.0; (90.7, 97.7) | N = 537; 94.4; (92.1, 96.2) | 0.6; (-3.9f, 3.9)
Study 2: NCT04707391.
hSBA = Serum bactericidal activity measured using an exogenous source of human complement, CI = Confidence interval, N = Number of participants, LOD = Limit of detection, LLOQ = Lower limit of quantitation.
a Per Protocol Set includes all participants in the Full Analysis Set minus participants with protocol deviations that lead to exclusion from the Per Protocol Set.
b Immune responses were measured one month after Dose 2 of PENMENVY or a single dose of MENVEO relative to baseline.
c Seroresponse is defined as: a post‑vaccination hSBA titer at least 4‑fold the LOD for participants with pre‑vaccination hSBA titer <LOD, a post‑vaccination hSBA titer at least 4‑fold the LLOQ for participants with pre‑vaccination hSBA titer ≥LOD and <LLOQ, and a post‑vaccination hSBA titer at least 4‑fold the pre‑vaccination hSBA titer for participants with pre‑vaccination hSBA titer ≥LLOQ.
d LOD = 5 for MenA; 4 for MenC, MenW, and MenY. LLOQ = 12 for MenA; 8 for MenC; 8 for MenW; 10 for MenY.
e CI calculated using Clopper‑Pearson method.
f Met predefined non‑inferiority criterion (lower limit of the 2‑sided 95% CI above -10% for vaccine group differences [PENMENVY minus MENVEO]). CI calculated using Miettinen and Nurminen method.

15 REFERENCES

1. Study 1 (NCT04502693), Study 2 (NCT04707391), Study 3 (NCT02212457), Study 4 (NCT02451514), Study 5 (NCT01272180), Study 6 (NCT01992536), Study 7 (NCT02946385), Study 8 (NCT02140762), Study 9 (NCT02285777), Study 10 (NCT01210885), Study 11 (NCT01367158), Study 12 (GSK Study V102P1)
2. Wang X, et al. Prevalence and genetic diversity of candidate vaccine antigens among invasive Neisseria meningitidis isolates in the United States. Vaccine. 2011; 29:4739‑4744.
3. Hosking J, et al. Immunogenicity, reactogenicity, and safety of a P1.7b,4 strain‑specific serogroup B meningococcal vaccine given to preteens. Clin Vaccine Immunol. 2007;14:1393‑1399.
4. Goldschneider I, Gotschlich EC, Artenstein MS. Human immunity to the meningococcus. I. The role of humoral antibodies. J Exp Med. 1969;129:1307‑1326.

16 HOW SUPPLIED/STORAGE AND HANDLING

16.1 How Supplied

PENMENVY is supplied in cartons containing:

- 10 vials of Lyophilized MenACWY Component (powder) and
- 10 prefilled TIP‑LOK syringes (Luer Lock syringes) of MenB Component (liquid) packaged without needles.

TIP‑LOK syringes are to be used with Luer Lock compatible needles.

The tip cap and rubber plunger of the prefilled syringe and the stopper of the vial are not made with natural rubber latex.

Table 8. Product Presentation for PENMENVY
Presentation | Carton NDC Number | Components
Presentation | Carton NDC Number | Lyophilized MenACWY Component (powder) | MenB Component; (liquid)
Carton of 10 doses | NDC 58160‑757‑15 | 10 Vials; NDC 58160‑730‑03 | 10 Prefilled syringes; NDC 58160‑750‑03

16.2 Storage Before Reconstitution

Store refrigerated, away from the freezer compartment, at 36°F to 46°F (2°C to 8°C).

Store in the original carton to protect from light.

Do not freeze. Discard if the carton has been frozen.

16.3 Storage After Reconstitution

Use immediately after reconstitution.

17 PATIENT COUNSELING INFORMATION

Give the patient, parent, or guardian the Vaccine Information Statements, which are required by the National Childhood Vaccine Injury Act of 1986 to be given prior to immunization. These materials are available free of charge at the Centers for Disease Control and Prevention (CDC) website (www.cdc.gov/vaccines).

Provide the following information to the vaccine recipient, parent, or guardian:

- Potential benefits and risks of immunization with PENMENVY.
- The importance of completing the immunization series.
- Potential for adverse reactions that have been temporally associated with administration of PENMENVY or other vaccines containing similar components.
- Advise them to report any adverse reactions to their healthcare provider, to GlaxoSmithKline at 1-888-825-5249, or through the Vaccine Adverse Event Reporting System (VAERS) at 1-800-822-7967 (or online at www.vaers.hhs.gov).

Trademarks are owned by or licensed to the GSK group of companies.

Manufactured by:
GSK Vaccines, Srl
Bellaria-Rosia 53018, Sovicille (SI), Italy
U.S. License No. 1617
Distributed by:
GlaxoSmithKline
Durham, NC 27701
©2025 GSK group of companies or its licensor.
PMV:2PI

PACKAGE LABEL

NDC 58160-757-15

PENMENVY

Meningoccal Groups A, B, C, W, and Y Vaccine

MenABCWY

Rx only

Notice: Lyophilized MenACWY Component and MenB Component must be combined before use.

10 Years through 25 Years of Age

Contents (10 doses of PENMENVY):

10 vials of Lyophilized MenaCWY Component

10 prefilled syringes of MenB Component

After reconstitution, a single dose of PENMENVY is approximately 0.5 mL

For intramuscular use

TIP-LOK syringes to be used with Luer Lock compatible needles

NEEDLES NOT INCLUDED

PENMENVY

©2025 GSK group of companies or its licensor.

Rev. 2/25

520997